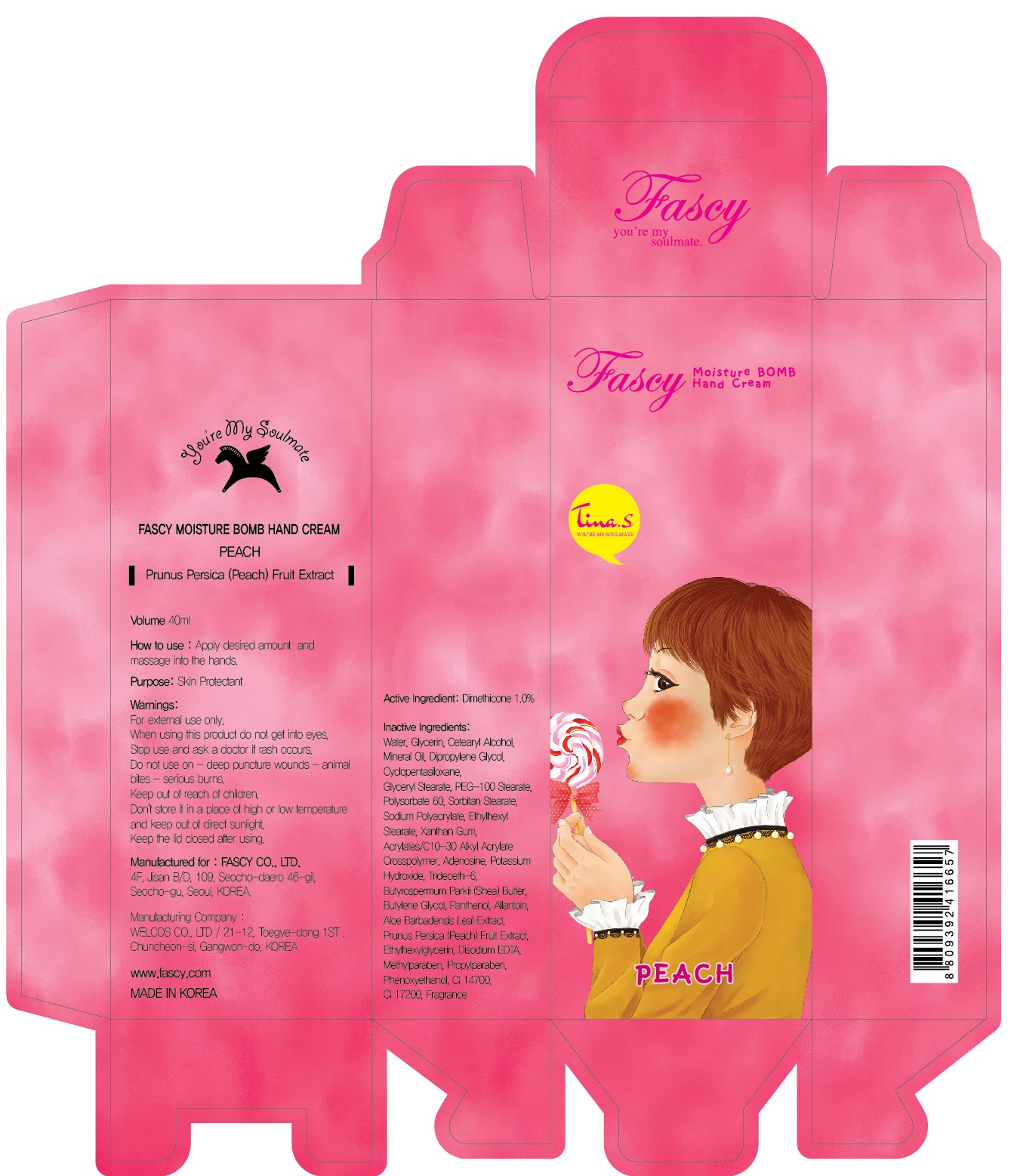 DRUG LABEL: Fascy Moisture Bomb Hand Peach 40mL
NDC: 70991-090 | Form: CREAM
Manufacturer: FASCY Co,.LTD.
Category: otc | Type: HUMAN OTC DRUG LABEL
Date: 20170310

ACTIVE INGREDIENTS: Dimethicone 0.4 g/40 mL
INACTIVE INGREDIENTS: Water; Glycerin

ACTIVE INGREDIENT

Active Ingredient: Dimethicone 1.0%

INACTIVE INGREDIENT

Inactive Ingredients: Water, Glycerin, Cetearyl Alcohol, Mineral Oil, Dipropylene Glycol, Cyclopentasiloxane, Glyceryl Stearate, PEG-100 Stearate, Polysorbate 60, Sorbitan Stearate, Sodium Polyacrylate, Ethylhexyl Stearate, Xanthan Gum, Acrylates/C10-30 Alkyl Acrylate Crosspolymer, Adenosine, Potassium Hydroxide, Trideceth-6, Butyrospermum Parkii (Shea) Butter, Butylene Glycol, Panthenol, Allantoin, Aloe Barbadensis Leaf Extract, Prunus Persica (Peach) Fruit Extract, Ethylhexylglycerin, Disodium EDTA, Methylparaben, Propylparaben, Phenoxyethanol, CI 14700, CI 17200, Fragrance

PURPOSE

Purpose: Skin Protectant

WARNINGS

Warnings: For external use only. When using this product do not get into eyes, Stop use and ask a doctor if rash occurs. Do not use on - deep puncture wounds - animal bites - serious burns. Keep out of reach of children. Do not keep it in direct sunlight, high or low temperature.

KEEP OUT OF REACH OF CHILDREN

How to use: Apply desired amount and massage into the hands.

How to use: Apply desired amount and massage into the hands.